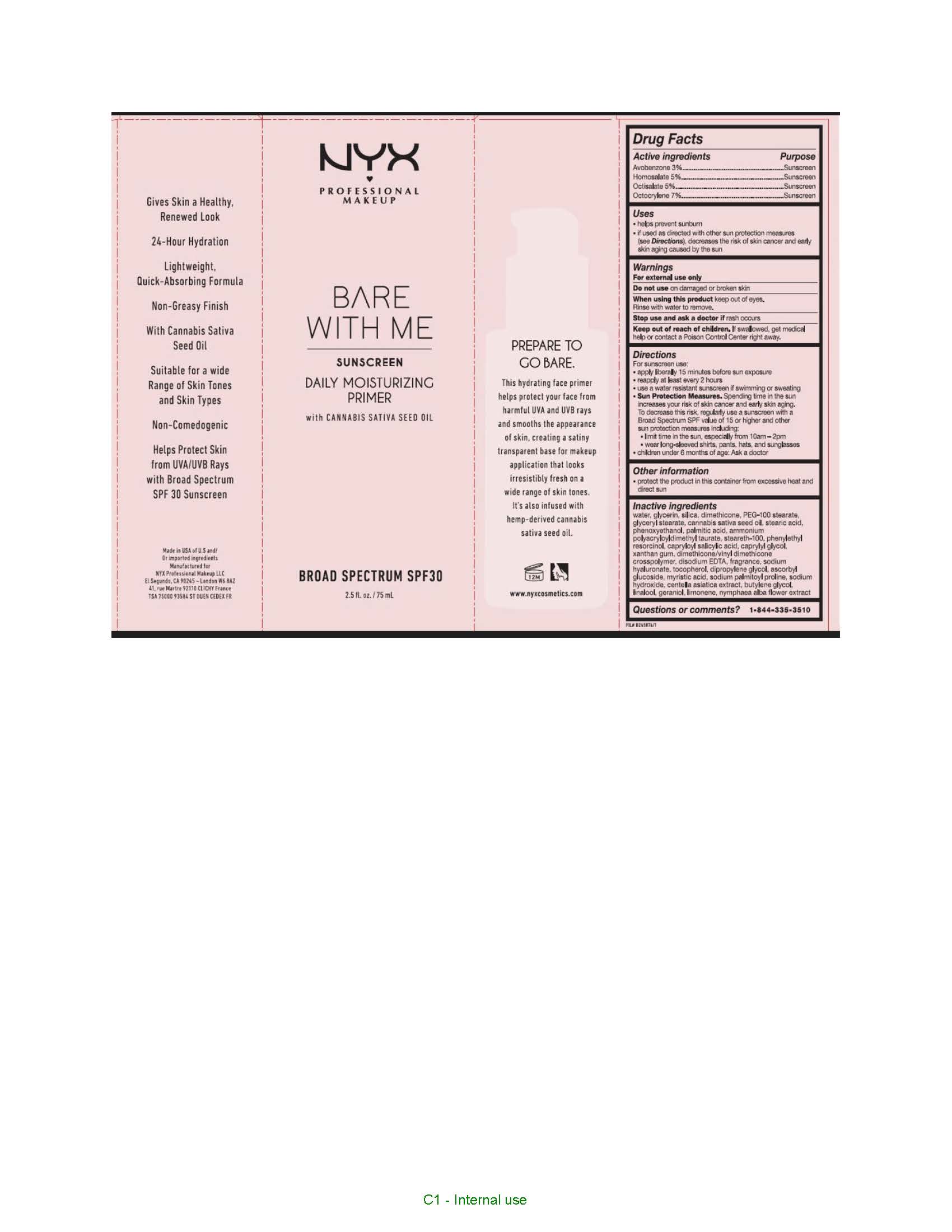 DRUG LABEL: NYX Professional Makeup Bare with Me Daily Moisturizing Primer with Cannabis Sativa Seed Oil SPF 30
NDC: 49967-217 | Form: CREAM
Manufacturer: L'Oreal USA Products Inc
Category: otc | Type: HUMAN OTC DRUG LABEL
Date: 20240116

ACTIVE INGREDIENTS: AVOBENZONE 30 mg/1 mL; HOMOSALATE 50 mg/1 mL; OCTISALATE 50 mg/1 mL; OCTOCRYLENE 70 mg/1 mL
INACTIVE INGREDIENTS: WATER; GLYCERIN; SILICON DIOXIDE; DIMETHICONE; PEG-100 STEARATE; GLYCERYL MONOSTEARATE; CANNABIS SATIVA SEED OIL; STEARIC ACID; PHENOXYETHANOL; PALMITIC ACID; AMMONIUM POLYACRYLOYLDIMETHYL TAURATE; STEARETH-100; PHENYLETHYL RESORCINOL; CAPRYLOYL SALICYLIC ACID; CAPRYLYL GLYCOL; XANTHAN GUM; DIMETHICONE/VINYL DIMETHICONE CROSSPOLYMER (SOFT PARTICLE); EDETATE DISODIUM; HYALURONATE SODIUM; TOCOPHEROL; DIPROPYLENE GLYCOL; ASCORBYL GLUCOSIDE; MYRISTIC ACID; SODIUM PALMITOYL PROLINE; SODIUM HYDROXIDE; CENTELLA ASIATICA; BUTYLENE GLYCOL; LINALOOL, (+)-; GERANIOL; LIMONENE, (+)-; NYMPHAEA ALBA FLOWER

Drug Facts

Active ingredients

Avobenzone 3%

Homosalate 5%

Octisalate 5%

Octocrylene 7%

Purpose

Sunscreen

Uses

- helps prevent sunburn
- if used as directed with other sun protection measures (see Directions), decreases the risk of skin cancer and early skin aging caused by the sun

Warnings

For external use only

Do not use

on damaged or broken skin

When using this product

keep out of eyes. Rinse with water to remove.

Stop use and ask a doctor if

rash occurs

Keep out of reach of children.

If swallowed, get medical help or contact a Poison Control Center right away.

Directions

For sunscreen use:

● apply liberally 15 minutes before sun exposure

● reapply at least every 2 hours

● use a water resistant sunscreen if swimming or sweating

● Sun Protection Measures. Spending time in the sun increases your risk of skin cancer and early skin aging. To decrease this risk, regularly use a sunscreen with a Broad Spectrum SPF value of 15 or higher and other sun protection measures including:

● limit time in the sun, especially from 10 a.m. – 2 p.m.

● wear long-sleeved shirts, pants, hats, and sunglasses

● children under 6 months of age: Ask a doctor

Other information

protect the product in this container from excessive heat and direct sun

Inactive ingredients

water, glycerin, silica, dimethicone, PEG-100 stearate, glyceryl stearate, cannabis sativa seed oil, stearic acid, phenoxyethanol, palmitic acid, ammonium polyacryloyldimethyl taurate, steareth-100, phenylethyl resorcinol, caprylyl salicylic acid, caprylyl glycol, xanthan gum, dimethicone/vinyl dimethicone crosspolymer, disodium EDTA, fragrance, sodium hyaluronate, tocopherol, dipropylene glycol, ascorbyl glucoside, myristic acid, sodium palmitoyl proline, sodium hydroxide, centella asiatica extract, butylene glycol, linalool, geraniol, limonene, nymphaea alba flower extract